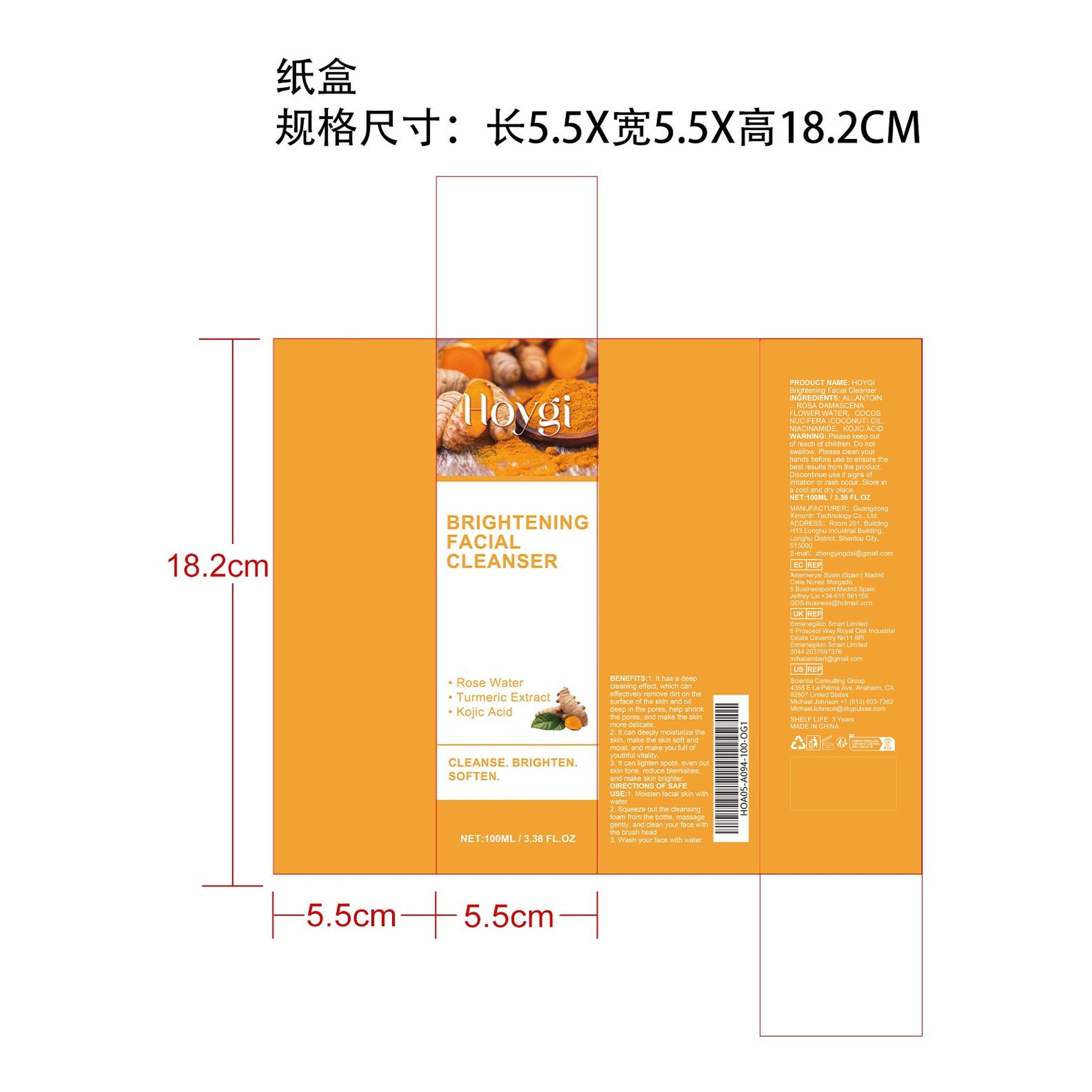 DRUG LABEL: HOYGI Brightening Facial Cleanser
NDC: 84660-035 | Form: CREAM
Manufacturer: Guangdong Ximonth Technology Co., Ltd.
Category: otc | Type: HUMAN OTC DRUG LABEL
Date: 20240926

ACTIVE INGREDIENTS: KOJIC ACID 10 mg/100 mg; COCONUT OIL 20 mg/100 mg; NIACINAMIDE 15 mg/100 mg; ROSA X DAMASCENA FLOWER OIL 25 mg/100 mg
INACTIVE INGREDIENTS: ALLANTOIN 30 mg/100 mg

Active Ingredient(s)

ROSA DAMASCENA FLOWER WATER、COCOS NUCIFERA (COCONUT) OIL、NIACINAMIDE、KOJIC ACID

Purpose

1. It has a deep cleaning effect, which can effectively remove dirt on the surface of the skin and oil deep in the pores, help shrink the pores, and make the skin more delicate.
2. It can deeply moisturize the skin, make the skin soft and moist, and make you full of youthful vitality.
3. It can lighten spots, even out skin tone, reduce blemishes, and make skin brighter.

Use

1. Moisten facial skin with water
2. Squeeze out the cleansing foam from the bottle, massage gently, and clean your face with the brush head
3. Wash your face with water

Warnings

Please keep out of reach of children.Do not swallow.Please clean your hands before use to ensure the best results from the product.Discontinue use if signs of irritation or rash occur.Store in a cool and dry place.

Do not use

Discontinue use if signs of irritation or rash occur.

STOP USE

Discontinue use if signs of irritation or rash occur.

KEEP OUT OF REACH OF CHILDREN

Please keep out of reach of children. Do not swallow.

STORAGE AND HANDLING

Avoid freezing and excessive heat above 40C (104F) ）
Store in a cool and dry place.

INACTIVE INGREDIENT

ALLANTOIN